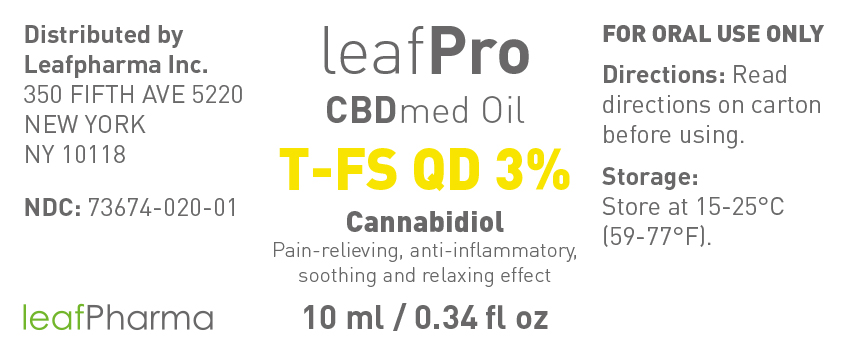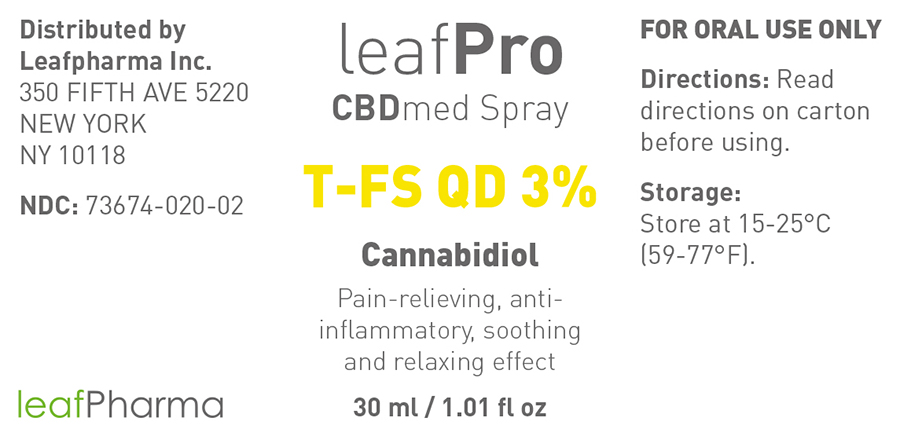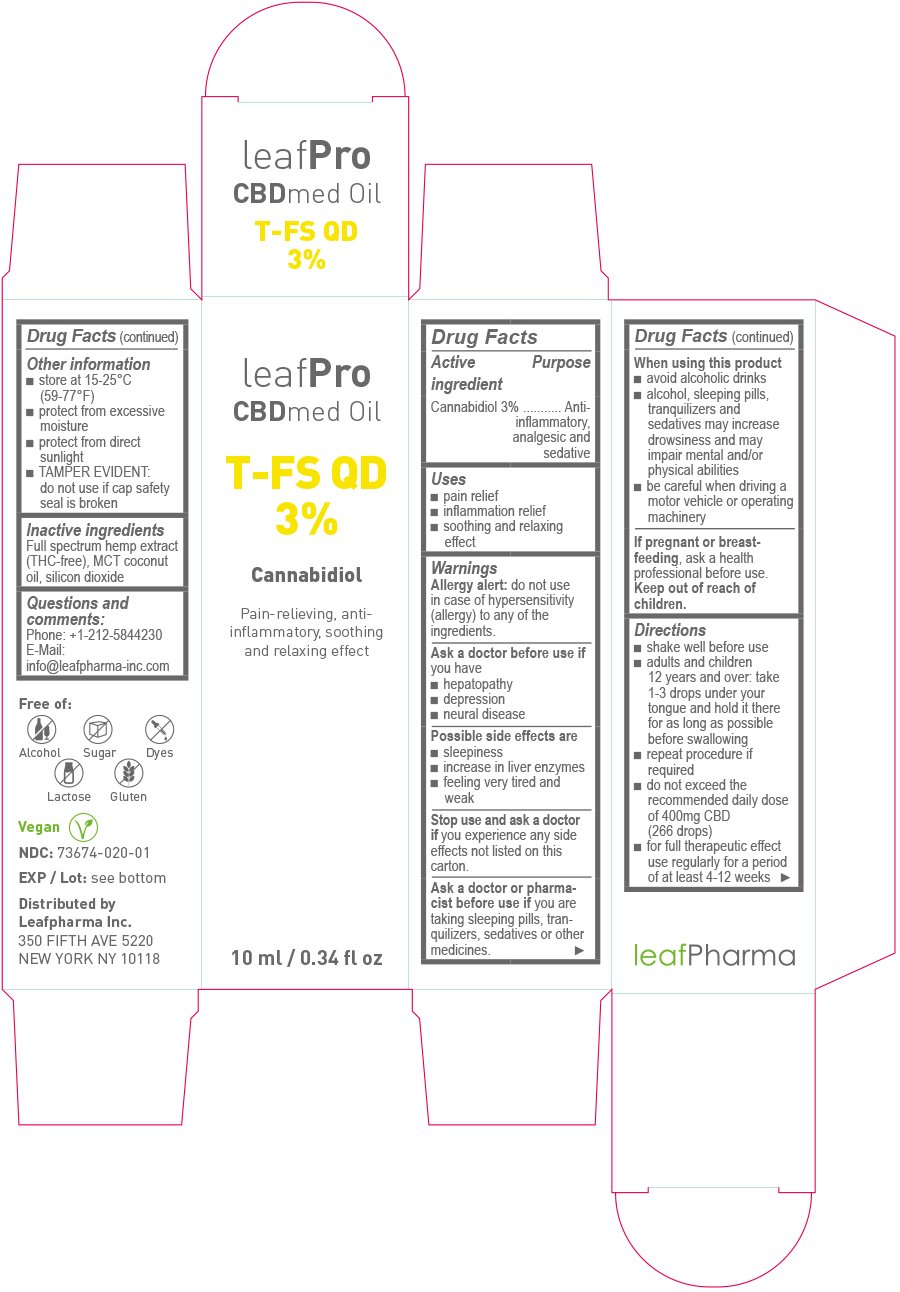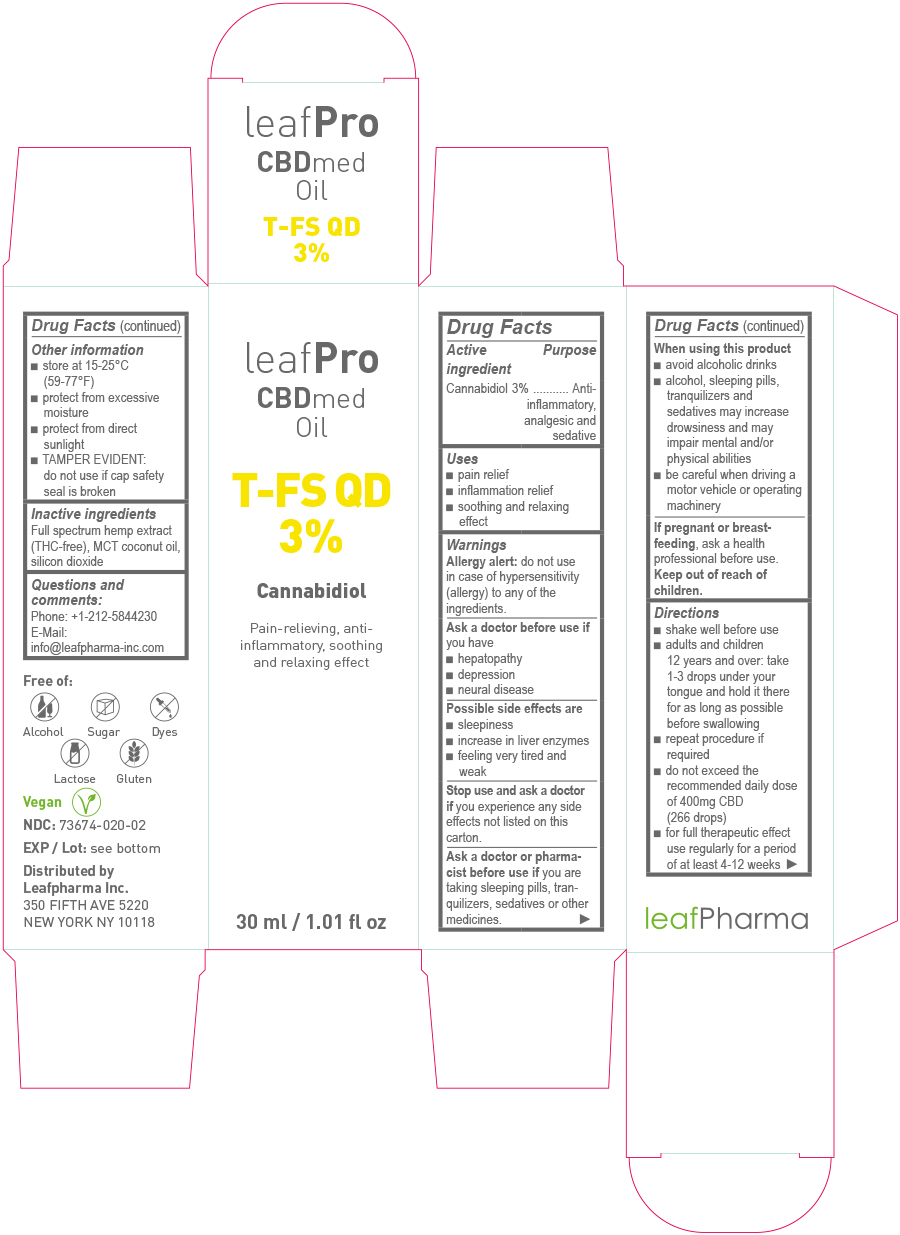 DRUG LABEL: leafPro CBDmed Oil T-FS QD 3%
NDC: 73674-020 | Form: OIL
Manufacturer: leafMed GmbH
Category: otc | Type: HUMAN OTC DRUG LABEL
Date: 20200313
DEA Schedule: CV

ACTIVE INGREDIENTS: CANNABIDIOL 3 g/100 mL
INACTIVE INGREDIENTS: HEMP; SILICON DIOXIDE; MEDIUM-CHAIN TRIGLYCERIDES

leafPro CBDmed Oil T-FS QD 3%

Drug Facts

Active Ingredient

Cannabidiol 3%

Purpose

Anti-inflammatory, analgesic and sedative

Uses

- pain relief
- inflammation relief
- soothing and relaxing effect

Warnings

Allergy alert:

do not use in case of hypersensitivity (allergy) to any of the ingredients.

Ask a doctor before use if

you have

- hepatopathy
- depression
- neural disease

Possible side effects are

- sleepiness
- increase in liver enzymes
- feeling very tired and weak

Stop use and ask a doctor if

you experience any side effects not listed on this carton.

Ask a doctor or pharmacist before use if

you are taking sleeping pills, tranquilizers, sedatives or other medicines.

When using this product

- avoid alcoholic drinks
- alcohol, sleeping pills, tranquilizers and sedatives may increase drowsiness and may impair mental and/or physical abilities
- be careful when driving a motor vehicle or operating machinery

If pregnant or breast-feeding,

ask a health professional before use.

Directions

- shake well before use
- adults and children 12 years and over: take 1 – 3 drops under your tongue and hold it there for as long as possible before swallowing
- repeat procedure if required
- do not exceed the recommended daily dose of 400mg CBD (266 drops)
- for full therapeutic effect use regularly for a period of at least 4-12 weeks

Other information

- store at 15-25°C (59-77°F)
- protect from excessive moisture
- protect from direct sunlight
- TAMPER EVIDENT: do not use if cap safety seal is broken

Inactive ingredients:

Full spectrum hemp extract (THC-free), MCT coconut oil, silicon dioxide

Questions and comments:

Phone: +1-212-5844230

E-Mail: info@leafpharma-inc.com

Principal Display Panel - 10ml

leaf Pro
CBDmed Oil
T-FS QD
3%
Cannabidiol
Pain-relieving, anti-inflammatory, soothing and relaxing effect
10ml / 0.34 fl oz

Principal Display Panel - 30ml

leaf Pro
CBDmed Oil
T-FS QD
3%
Cannabidiol
Pain-relieving, anti-inflammatory, soothing and relaxing effect
30ml / 1.01 fl oz